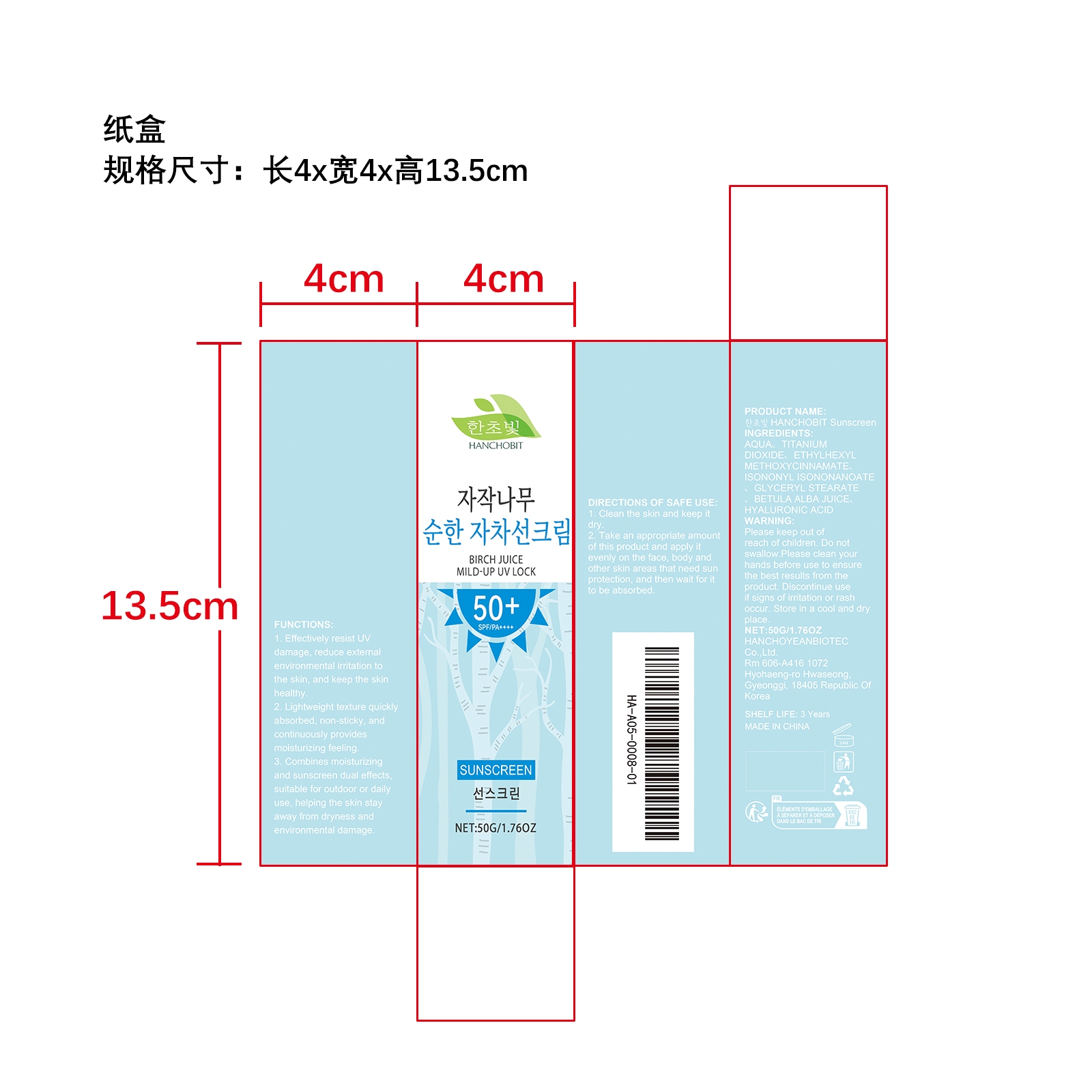 DRUG LABEL: HANCHOBIT Sunscreen
NDC: 85164-005 | Form: CREAM
Manufacturer: HANCHOYEANBIOTEC Co.,Ltd.
Category: otc | Type: HUMAN OTC DRUG LABEL
Date: 20251127

ACTIVE INGREDIENTS: BETULA ALBA JUICE 0.01 mg/50 mg
INACTIVE INGREDIENTS: ISONONYL ISONONANOATE 2 mg/50 mg; HYALURONIC ACID 0.01 mg/50 mg; GLYCERYL STEARATE 0.5 mg/50 mg; AQUA 37.98 mg/50 mg; ETHYLHEXYL METHOXYCINNAMATE 4.5 mg/50 mg; TITANIUM DIOXIDE 5 mg/50 mg

ACTIVE INGREDIENT

BETULA ALBA JUICE

PURPOSE

1. Effectively resist UV damage, reduce external environmental irritation to the skin, and keep the skin healthy.

2. Lightweight texture quickly absorbed, non-sticky, and continuously provides moisturizing feeling.

3. Combines moisturizing and sunscreen dual effects, suitable for outdoor or daily use, helping the skin stay away from dryness and environmental damage.

WHEN USING

1. Clean the skin and keep it dry.

2. Take an appropriate amount of this product and apply it evenly on the face, body and other skin areas that need sun protection, and then wait for it to be absorbed.

WARNINGS

Please keep out of reach of children. Do not swallow.Please clean your hands before use to ensure the best results from the product. Discontinue use if signs of irritation or rash occur. Store in a cool and dry place.

DO NOT USE

Discontinue use if signs of irritation or rash occur.

STOP USE

Discontinue use if signs of irritation or rash occur.

KEEP OUT OF REACH OF CHILDREN

Please keep out of reach of children. Do not swallow.

STORAGE AND HANDLING

Store in a cool and dry place.

INACTIVE INGREDIENT

AQUA、TITANIUM DIOXIDE、ETHYLHEXYL METHOXYCINNAMATE、ISONONYL ISONONANOATE、GLYCERYL STEARATE、HYALURONIC ACID

INDICATIONS AND USAGE

1. Clean the skin and keep it dry.

2. Take an appropriate amount of this product and apply it evenly on the face, body and other skin areas that need sun protection, and then wait for it to be absorbed.

DOSAGE AND ADMINISTRATION

1. Clean the skin and keep it dry.

2. Take an appropriate amount of this product and apply it evenly on the face, body and other skin areas that need sun protection, and then wait for it to be absorbed.